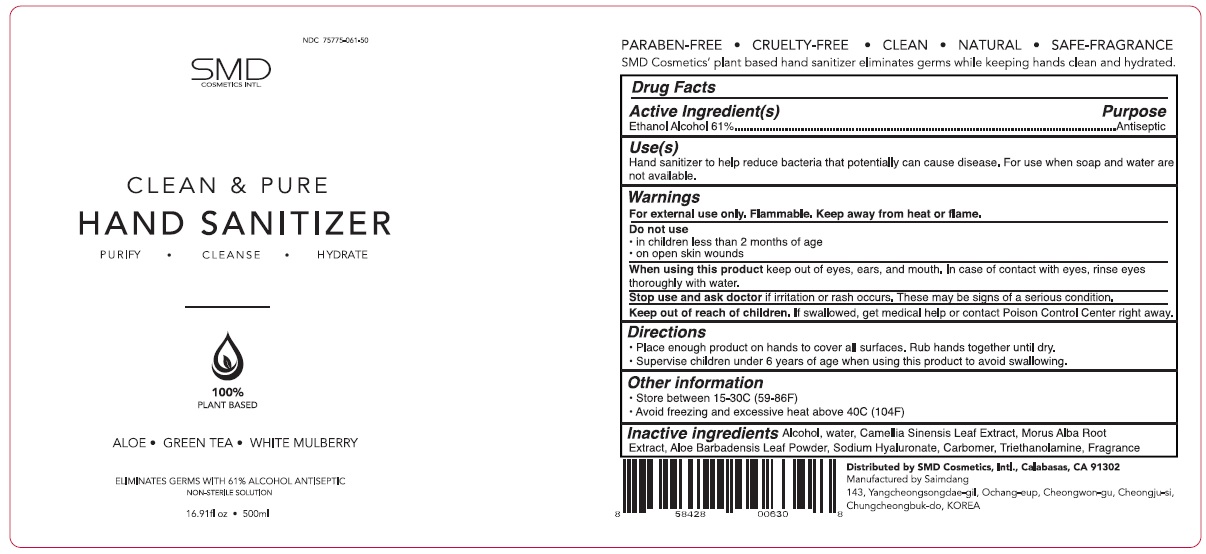 DRUG LABEL: SMD Cosmetics Clean and Pure Hand Sanitizer
NDC: 75775-061 | Form: SOLUTION
Manufacturer: Smd Cosmetics, Inc.
Category: otc | Type: HUMAN OTC DRUG LABEL
Date: 20200508

ACTIVE INGREDIENTS: ALCOHOL 61 mL/100 mL
INACTIVE INGREDIENTS: WATER; GREEN TEA LEAF; MORUS ALBA ROOT; ALOE VERA LEAF; HYALURONATE SODIUM; CARBOMER HOMOPOLYMER, UNSPECIFIED TYPE; TROLAMINE

SMD Cosmetics Clean and Pure Hand Sanitizer

Active Ingredient(s)

Ethanol 61%

Purpose

Antiseptic

Use(s)

Hand sanitizer to help reduce bacteria that potentially can cause disease. For use when soap and water are not available.

Warnings

For external use only. Flammable. Keep away from heat or flame

Do not use

- in children less than 2 months of age
- on open skin wounds

When using this product keep out of eyes, ears, and mouth. In case of contact with eyes, rinse eyes thoroughly with water.

Stop use and ask doctor if irritation or rash occurs. These may be signs of a serious condition.

Keep out of reach of Children. If swallowed, get medical help or contact Poison Control Center right away.

Directions

• Place enough product on hands to cover all surfaces. Rub hands together until dry.

• Supervise children under 6 years of age when using this product to avoid swallowing.

Other information

• Store between 15-30C (59-86F)

• Avoid freezing and excessive heat above 40C (104F)

INACTIVE INGREDIENT

Inactive ingredients Water, Camellia Sinensis Leaf Extract, Morus Alba Root Extract, Aloe Barbadensis Leaf Powder, Sodium Hyaluronate, Carbomer, Triethanolamine, Fragrance

PURIFY • CLEANSE • HYDRATE

100% PLANT BASED

ALOE • GREEN TEA • WHITE MULBERRY

ELIMINATES GERMS WITH 61% ALCOHOL ANTISEPTIC

NON-STERILE SOLUTION

PARABEN-FREE • CRUELTY-FREE • CLEAN • NATURAL • SAFE-FRAGRANCE

SMD Cosmetics’ plant based hand sanitizer eliminates germs while keeping hands clean and hydrated.

Distributed by SMD Cosmetics, Intl., Calabasas, CA 91302

Manufactured by Saimdang

143, Yangcheongsongdae-gil, Ochang-eup, Cheongwon-gu, Cheongju-si,

Chungcheongbuk-do, KOREA